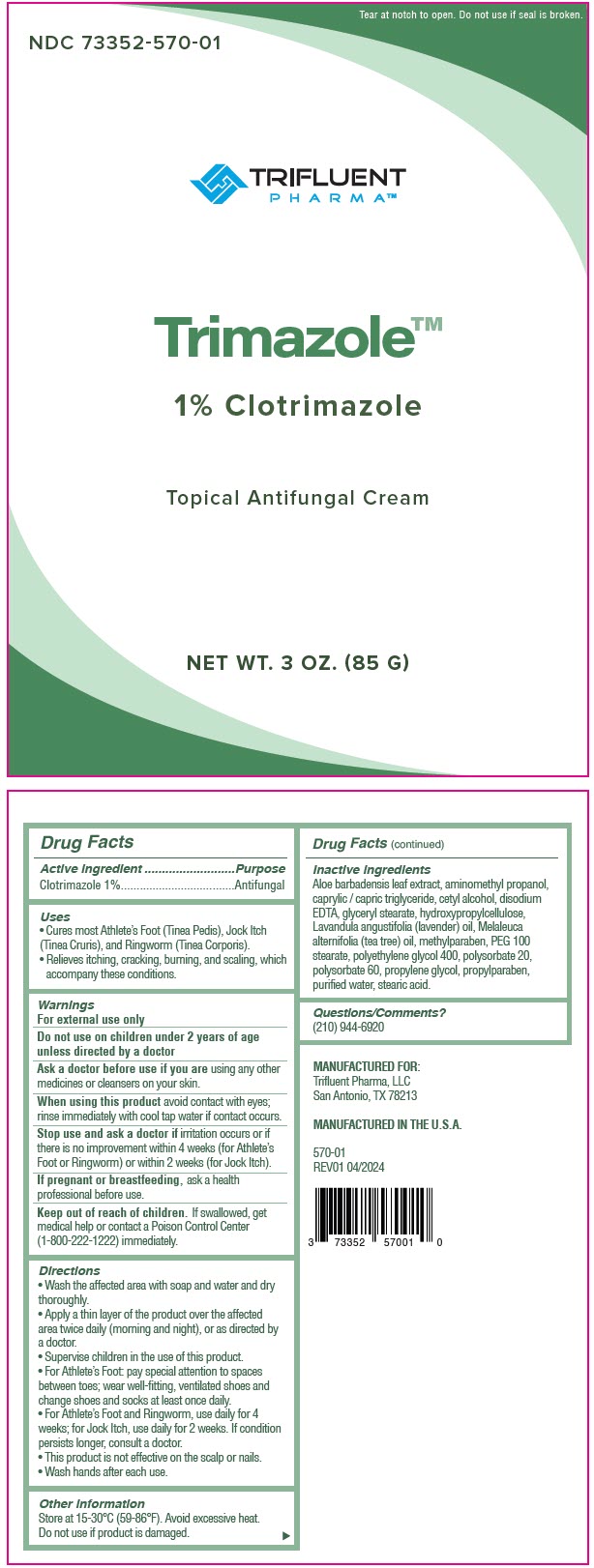 DRUG LABEL: Trimazole
NDC: 73352-570 | Form: CREAM
Manufacturer: Trifluent Pharma LLC
Category: otc | Type: HUMAN OTC DRUG LABEL
Date: 20251201

ACTIVE INGREDIENTS: CLOTRIMAZOLE 1 g/100 g
INACTIVE INGREDIENTS: ALOE VERA LEAF; AMINOMETHYLPROPANOL; MEDIUM-CHAIN TRIGLYCERIDES; CETYL ALCOHOL; EDETATE DISODIUM; GLYCERYL MONOSTEARATE; HYDROXYPROPYL CELLULOSE, UNSPECIFIED; LAVENDER OIL; TEA TREE OIL; METHYLPARABEN; PEG-100 MONOSTEARATE; POLYETHYLENE GLYCOL 400; POLYSORBATE 20; POLYSORBATE 60; PROPYLENE GLYCOL; PROPYLPARABEN; WATER; STEARIC ACID

Trimazole™

Drug Facts

Active ingredient

Clotrimazole 1%

Purpose

Antifungal

Uses

- Cures most Athlete's Foot (Tinea Pedis), Jock Itch (Tinea Cruris), and Ringworm (Tinea Corporis).
- Relieves itching, cracking, burning, and scaling, which accompany these conditions.

Warnings

For external use only

Do not use on children under 2 years of age unless directed by a doctor

Ask a doctor before use if you are using any other medicines or cleansers on your skin.

When using this product avoid contact with eyes; rinse immediately with cool tap water if contact occurs.

Stop use and ask a doctor if irritation occurs or if there is no improvement within 4 weeks (for Athlete's Foot or Ringworm) or within 2 weeks (for Jock Itch).

PREGNANCY OR BREAST FEEDING

If pregnant or breastfeeding, ask a health professional before use.

Keep out of reach of children. If swallowed, get medical help or contact a Poison Control Center (1-800-222-1222) immediately.

Directions

- Wash the affected area with soap and water and dry thoroughly.
- Apply a thin layer of the product over the affected area twice daily (morning and night), or as directed by a doctor.
- Supervise children in the use of this product.
- For Athlete's Foot: pay special attention to spaces between toes; wear well-fitting, ventilated shoes and change shoes and socks at least once daily.
- For Athlete's Foot and Ringworm, use daily for 4 weeks; for Jock Itch, use daily for 2 weeks. If condition persists longer, consult a doctor.
- This product is not effective on the scalp or nails.
- Wash hands after each use.

Other information

Store at 15-30°C (59-86°F). Avoid excessive heat.

Do not use if product is damaged.

Inactive ingredients

Aloe barbadensis leaf extract, aminomethyl propanol, caprylic / capric triglyceride, cetyl alcohol, disodium EDTA, glyceryl stearate, hydroxypropylcellulose, Lavandula angustifolia (lavender) oil, Melaleuca alternifolia (tea tree) oil, methylparaben, PEG 100 stearate, polyethylene glycol 400, polysorbate 20, polysorbate 60, propylene glycol, propylparaben, purified water, stearic acid.

Questions/Comments?

(210) 944-6920

PRINCIPAL DISPLAY PANEL - 85 G Tube Pouch Label

Tear at notch to open. Do not use if seal is broken.

NDC 73352-570-01

TRIFLUENT
PHARMA™

Trimazole™

1% Clotrimazole

Topical Antifungal Cream

NET WT. 3 OZ. (85 G)